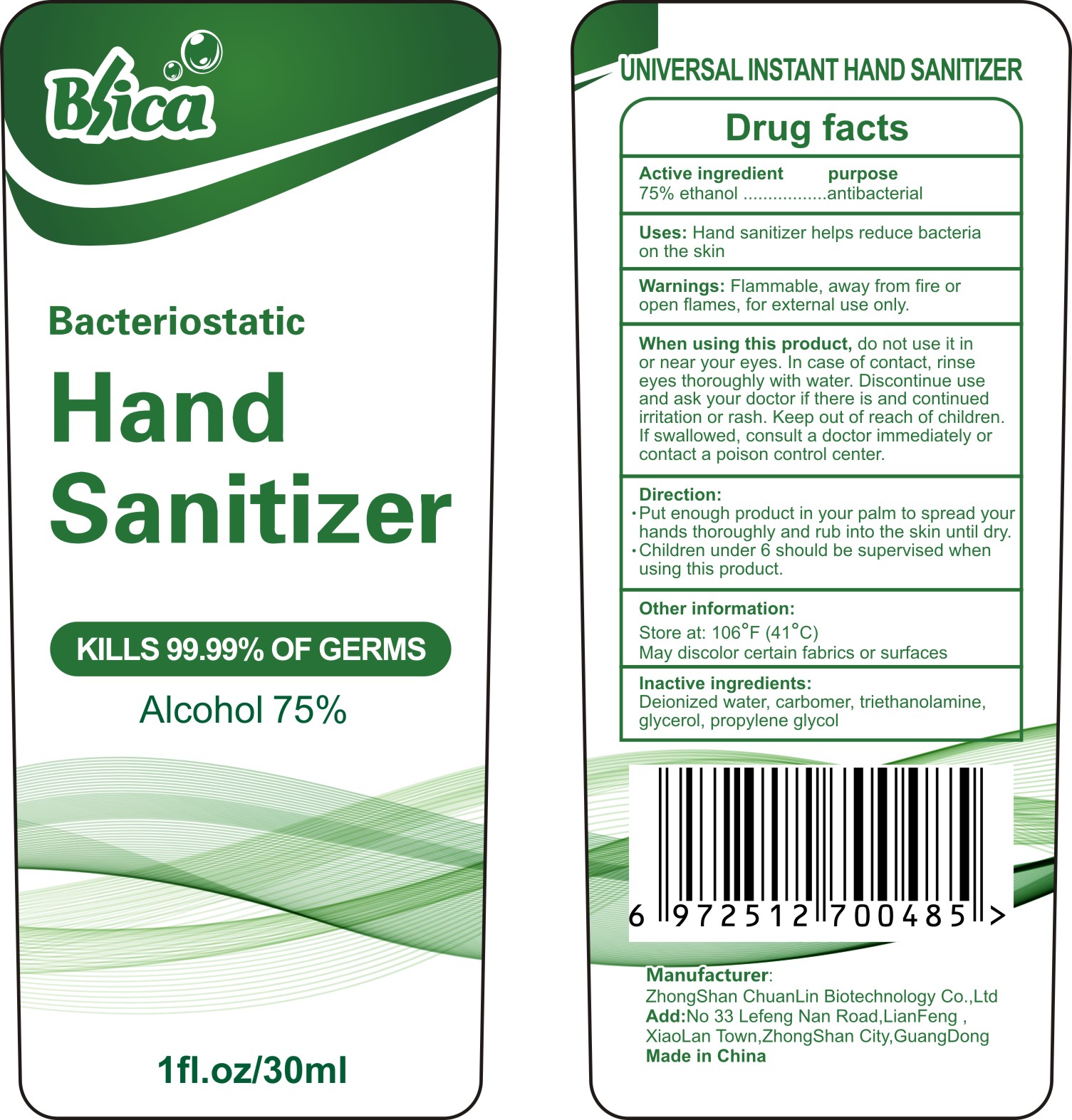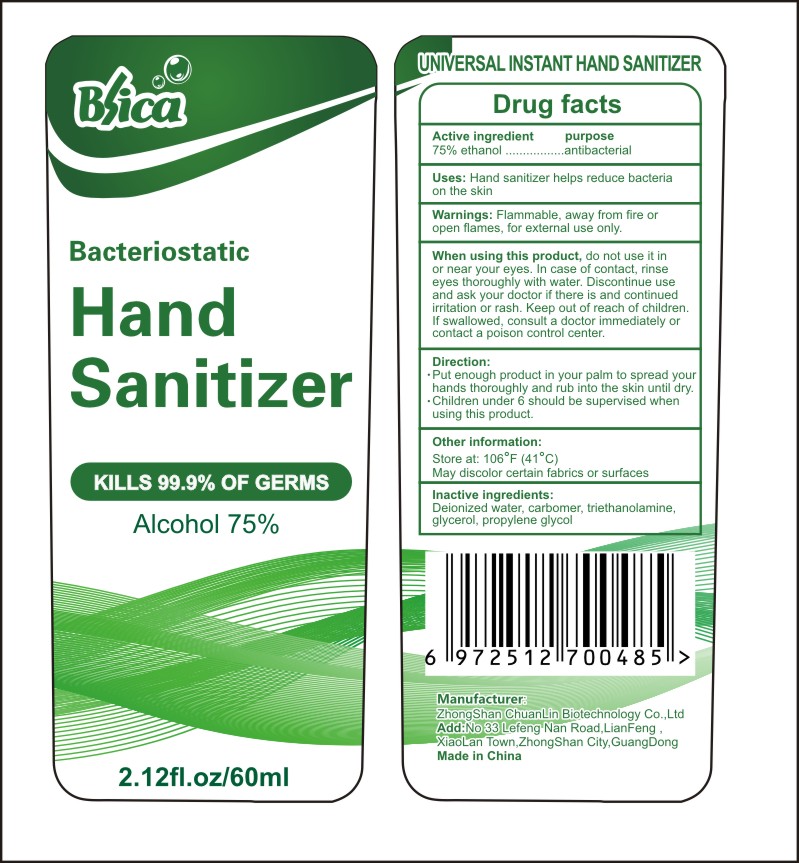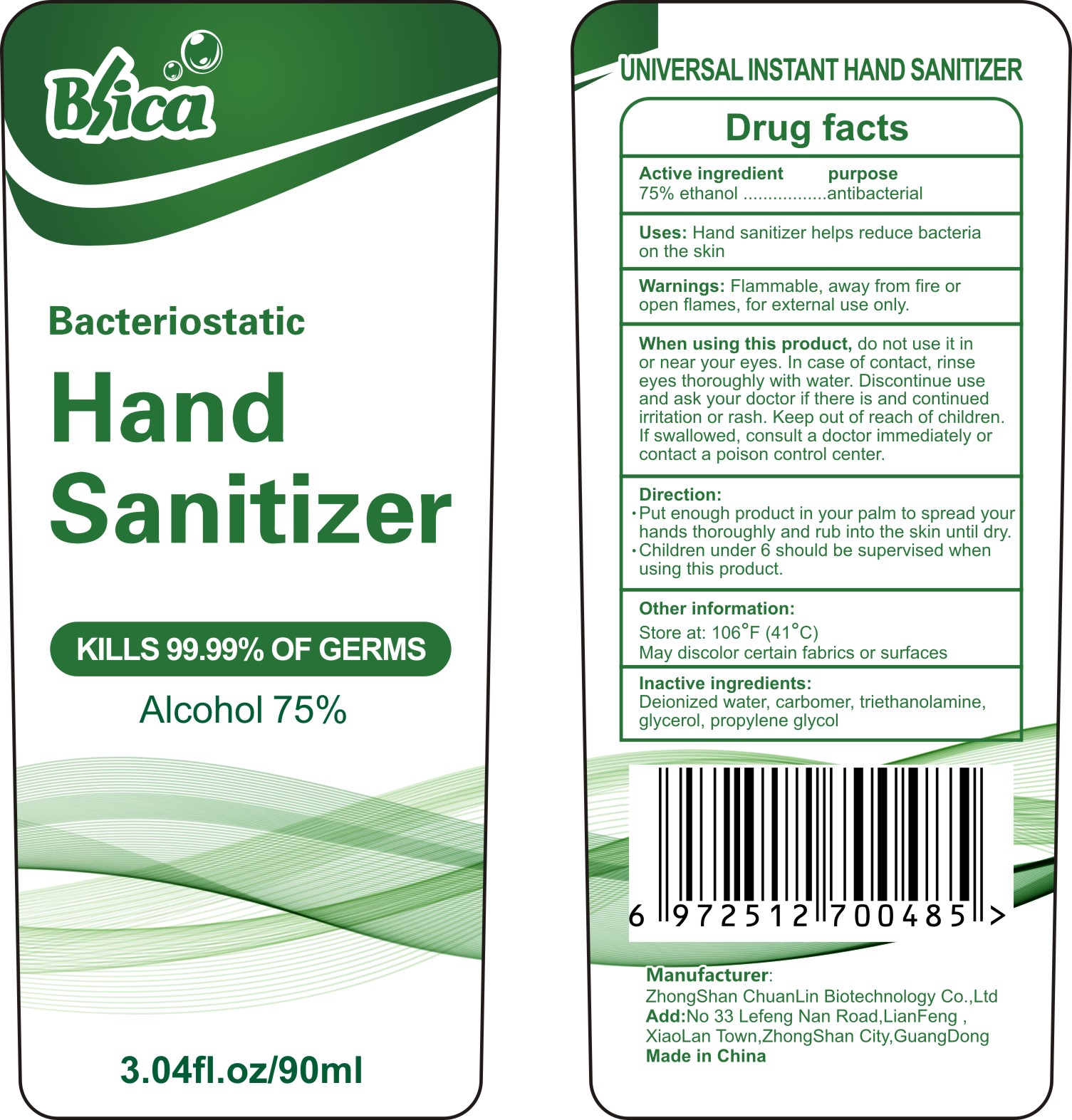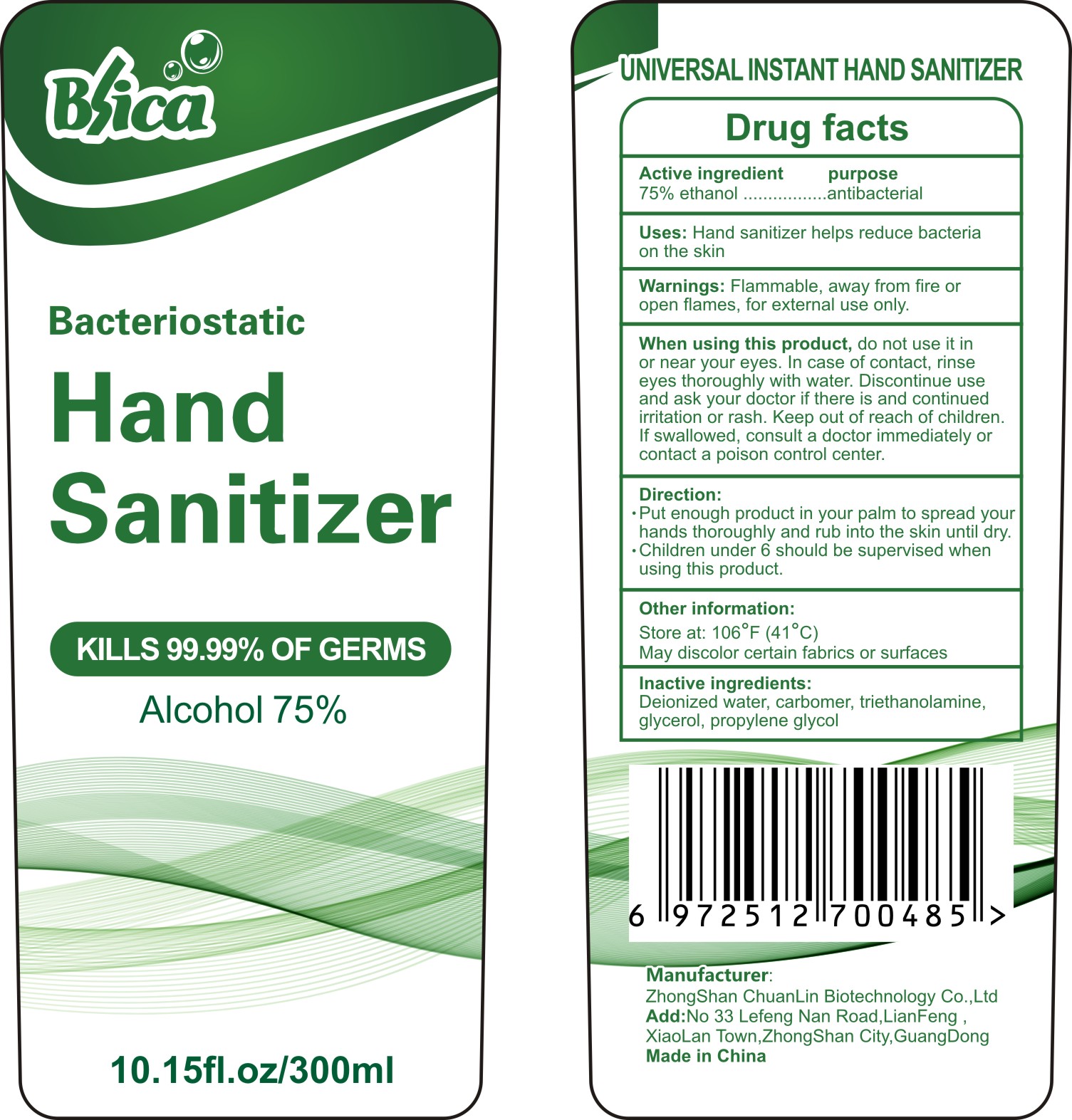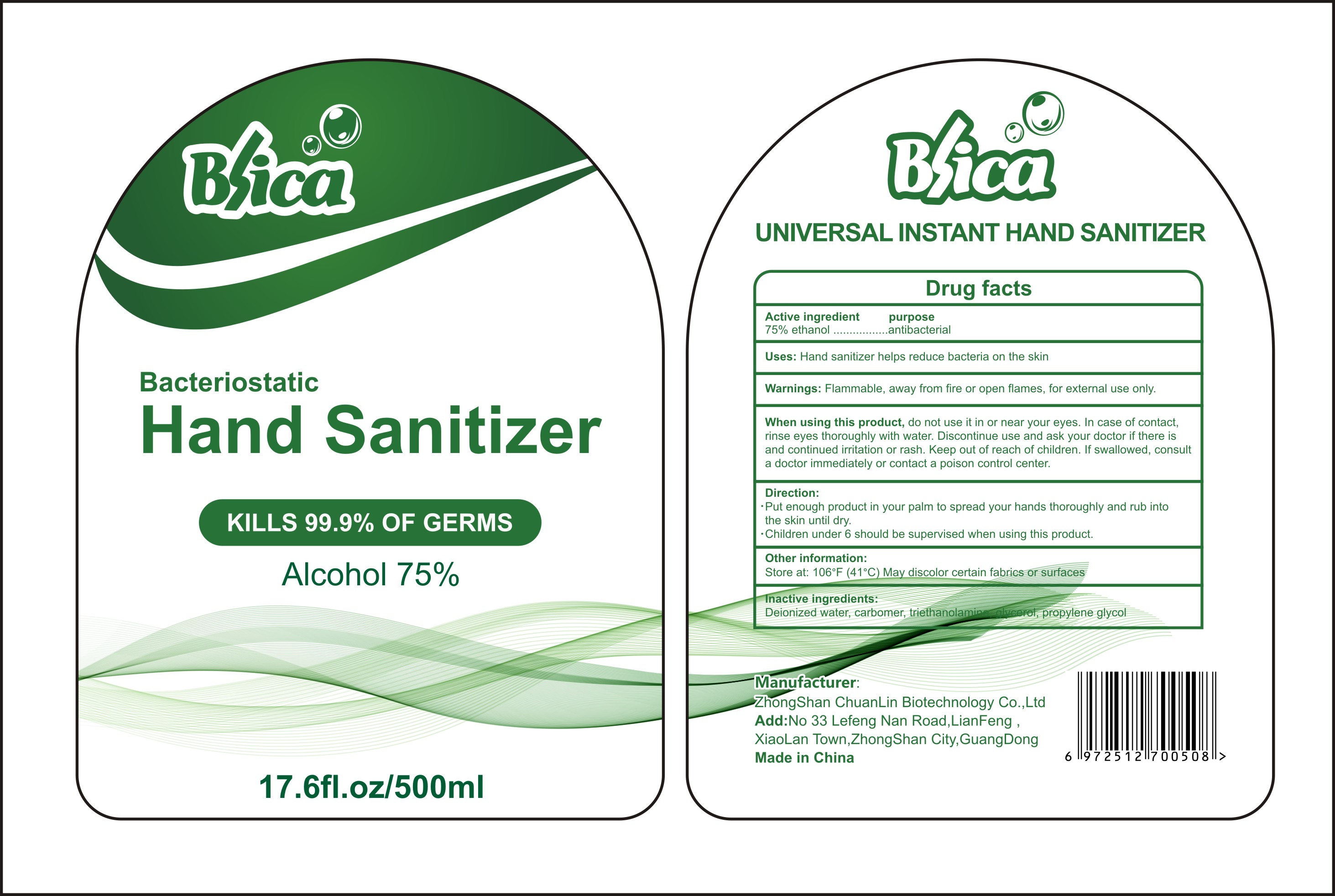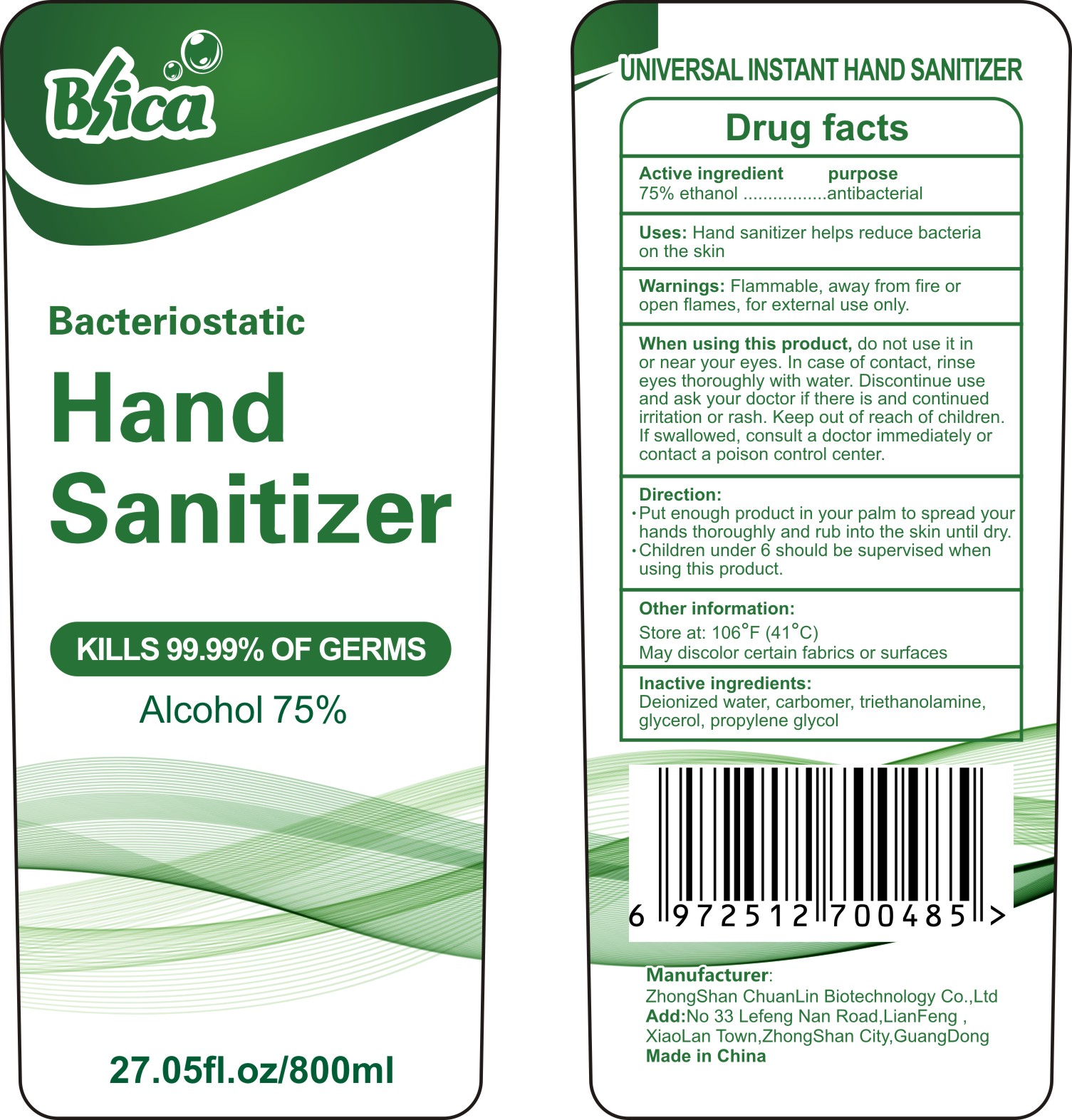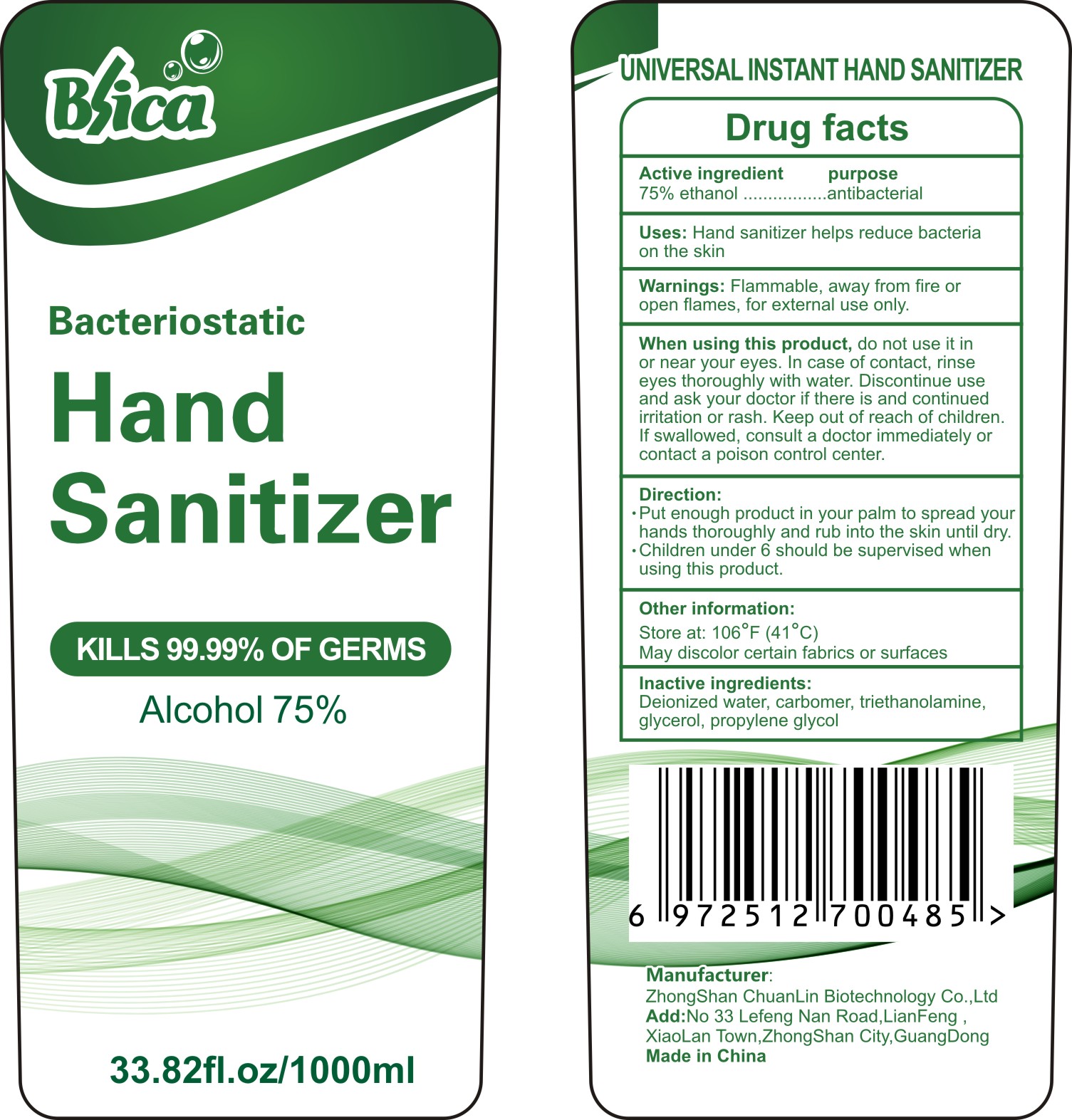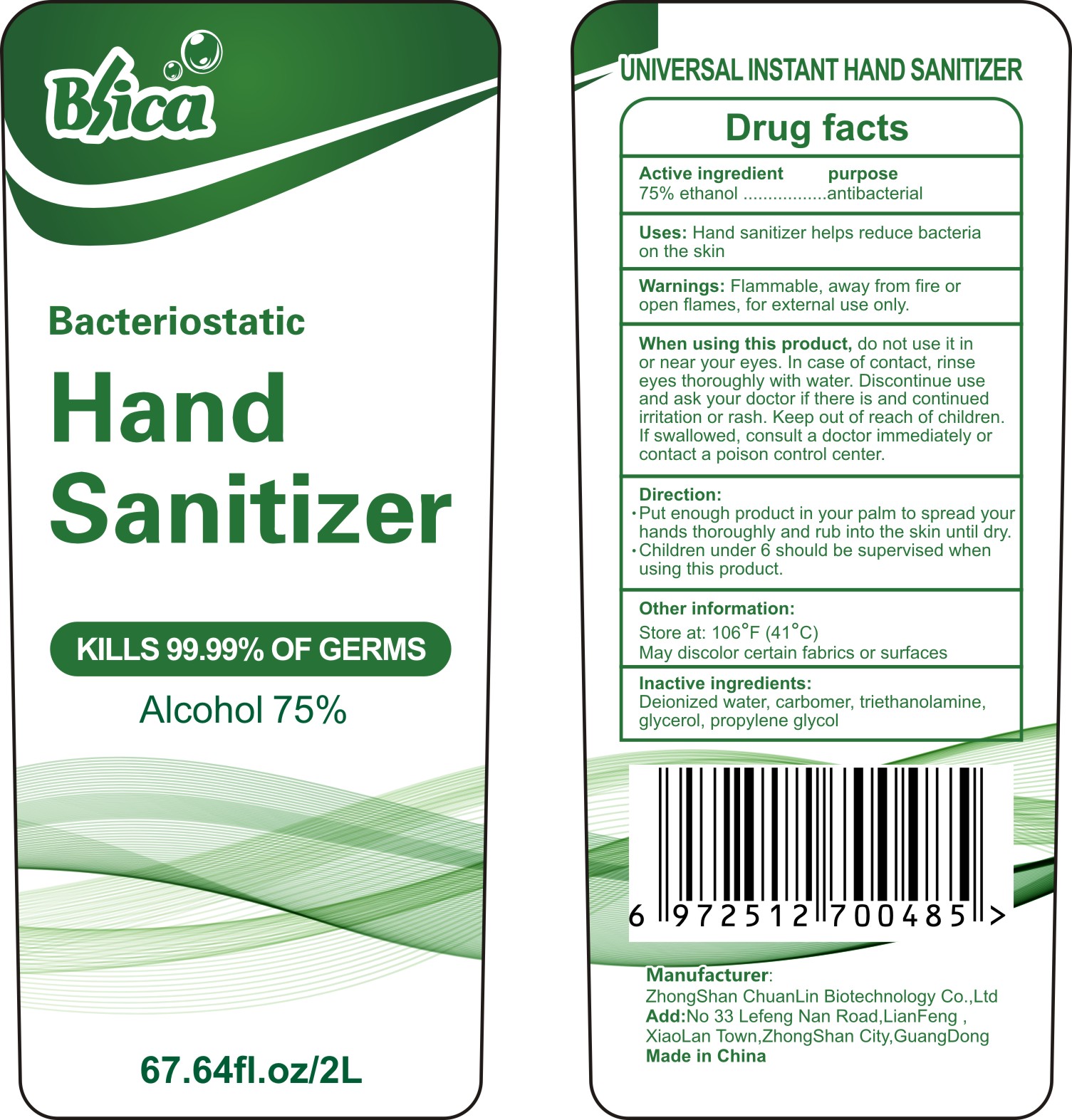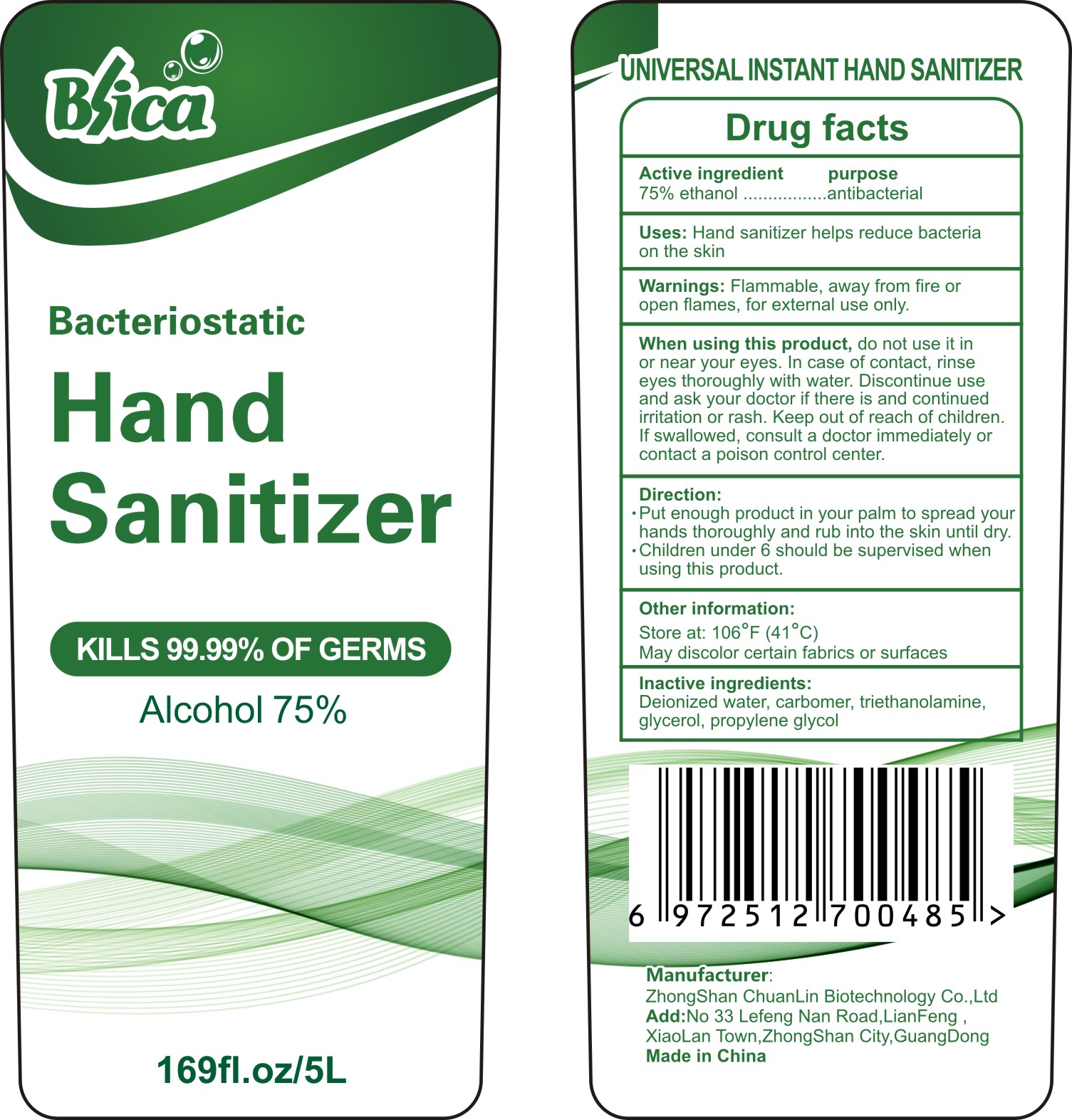 DRUG LABEL: Hand Sanitizer
NDC: 75142-001 | Form: GEL
Manufacturer: Zhongshan Chuanlin Biotechnology Co., Ltd.
Category: otc | Type: HUMAN OTC DRUG LABEL
Date: 20200419

ACTIVE INGREDIENTS: ALCOHOL 75 mL/100 mL
INACTIVE INGREDIENTS: CARBOMER HOMOPOLYMER, UNSPECIFIED TYPE; GLYCERIN; TROLAMINE; PROPYLENE GLYCOL; WATER

Hand Sanitizer

Active ingredient

75% ethanol

purpose

antibacterial

Uses

Hand sanitizer helps reduce bacteria on the skin.

Warnings

Flammable,away from fire or open flames, for external use only.

When using this product

do not use it in or near your eyes.In case of contact, rinse eyes thoroughly with water.Discontinue use and ask your doctor if there is and continued irritation or rash.Keep out of reach of children.If swallowed,consult a doctor immediately or contact a poison control center.

Directions

Put enough product in your palm to spread your hands

thoroughly and rub into the skin until dry.

Children under 6 should be supervised when using this product.

Other information

Store at：106°F(41°C)

May discolor certain fabrics or surfaces

Inactive ingredients

Deionized water, carbomer,

triethanolamine,glycerol,propylene glycol